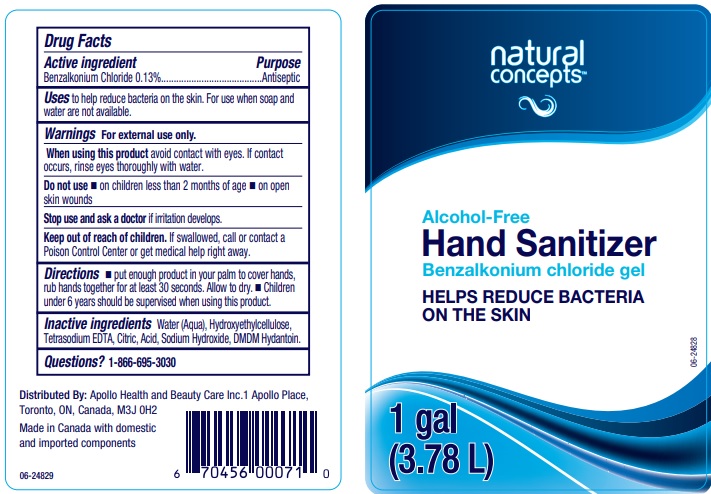 DRUG LABEL: Natural Concepts Alcohol-Free Hand Sanitizer
NDC: 63148-512 | Form: GEL
Manufacturer: Apollo Health and Beauty Care Inc.
Category: otc | Type: HUMAN OTC DRUG LABEL
Date: 20200717

ACTIVE INGREDIENTS: BENZALKONIUM CHLORIDE 1.3 mg/1 mL
INACTIVE INGREDIENTS: WATER; HYPROMELLOSES; EDETATE SODIUM; CITRIC ACID MONOHYDRATE; SODIUM HYDROXIDE; DMDM HYDANTOIN

Drug Facts

Active ingredient

Benzalkonium Chloride 0.13%

Purpose

Antiseptic

Uses

to help reduce bacteria on the skin. For use when soap and water are not available.

Warnings

For external use only.

When using this product

avoid contact with eyes. If contact occurs, rinse eyes thoroughly with water.

Do not use

- on children less than 2 months of age
- on open skin wounds

Stop use and ask a doctor if

irritation develops.

Keep out of reach of children.

If swallowed, call or contact a Poison Control Center or get medical help right away.

Directions

- put enough product in your palm to cover hands, rub hands together for at least 30 seconds. Allow to dry.
- Children under 6 years should be supervised when using this product.

Inactive ingredients

Water (Aqua), Hydroxyethylcellulose, Tetrasodium EDTA, Citric Acid, Sodium Hydroxide, DMDM Hydantoin.

Questions?

1-866-695-3030